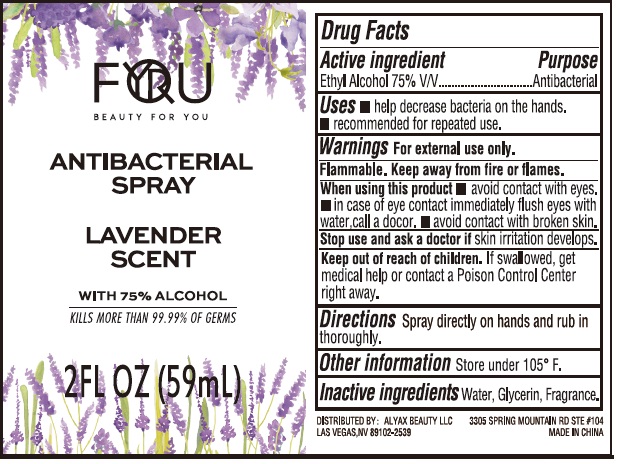 DRUG LABEL: Antibacterial Hand Sanitizer Lavender scent
NDC: 74149-032 | Form: SPRAY
Manufacturer: Yiwu Yangjie Daily Chemicals Co.,Ltd.
Category: otc | Type: HUMAN OTC DRUG LABEL
Date: 20200828

ACTIVE INGREDIENTS: alcohol 75 mL/100 mL
INACTIVE INGREDIENTS: WATER; GLYCERIN

Drug facts

Active ingredient Ethyl Alcohol ........... 75% v/v

PURPOSE

Antibacterial

KEEP OUT OF REACH OF CHILDREN

If swallowed, get medical help or contact a poison control center right away.

INDICATIONS AND USAGE

- Help decrease bacteria on the hands.
- recommended for repeated use

WARNINGS

For external use only
Flammable. Keep away from fire or flame.

When using this product

- avoid contact with eyes and nose.
- In case of contact flush eyes with water, call a doctor
- avoi contact with broken skin.

Stop use and ask a doctor If irritation develops.

Other information:

Store under 105℉.

DOSAGE AND ADMINISTRATION

Spray directly on hands and rub in thoroughly.

INACTIVE INGREDIENT

Water, Glycerin, Fragrance